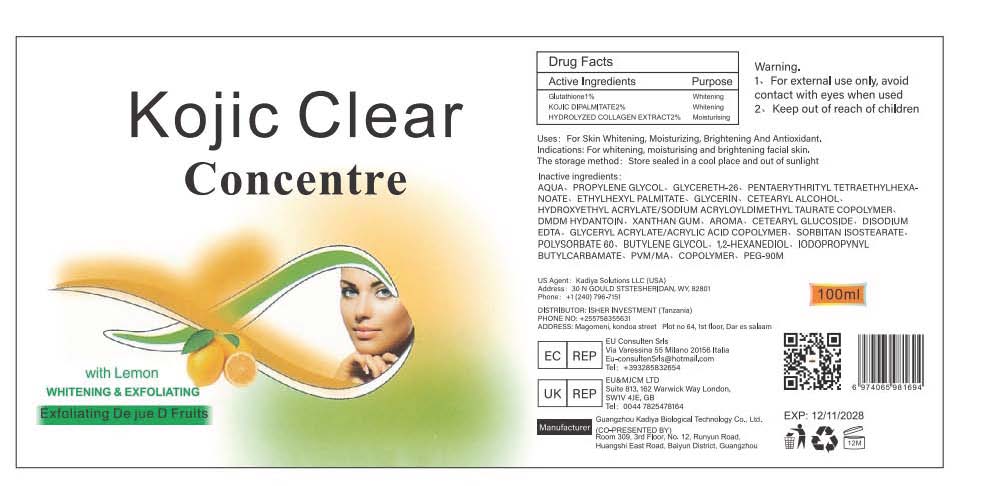 DRUG LABEL: Kojic Clear Concentre
NDC: 84423-066 | Form: CREAM, AUGMENTED
Manufacturer: Guangzhou Kadiya Biotechnology Co., Ltd.
Category: otc | Type: HUMAN OTC DRUG LABEL
Date: 20250217

ACTIVE INGREDIENTS: GLUTATHIONE 1 g/100 mL; KOJIC DIPALMITATE 2 g/100 mL
INACTIVE INGREDIENTS: GLYCERETH-26; GLYCERIN; CETEARYL ALCOHOL; HYDROXYETHYL ACRYLATE/SODIUM ACRYLOYLDIMETHYL TAURATE COPOLYMER (45000 MPA.S AT 1%); 1,2-HEXANEDIOL; DMDM HYDANTOIN; PENTAERYTHRITYL TETRAETHYLHEXANOATE; METHYL VINYL ETHER AND MALEIC ANHYDRIDE COPOLYMER (1100000 WAMW); XANTHAN GUM; CETEARYL GLUCOSIDE; BUTYLENE GLYCOL; PEG-90M; EDETATE DISODIUM; GLYCERYL ACRYLATE/ACRYLIC ACID COPOLYMER (300000 CP AT 2%); POLYSORBATE 60; SORBITAN ISOSTEARATE; ETHYLHEXYL PALMITATE; AQUA; PROPYLENE GLYCOL; IODOPROPYNYL BUTYLCARBAMATE

PURPOSE

For Skin Whitening, Moisturizing, Brightening And Antioxidant.

INACTIVE INGREDIENT

AQUA、PROPYLENE GLYCOL、GLYCERETH-26、PENTAERYTHRITYL TETRAETHYLHEXANOATE、ETHYLHEXYL PALMITATE、GLYCERIN、CETEARYL ALCOHOL、HYDROXYETHYL ACRYLATE/SODIUM ACRYLOYLDIMETHYL TAURATE COPOLYMER、DMDM HYDANTOIN、XANTHAN GUM、AROMA、CETEARYL GLUCOSIDE、DISODIUM EDTA、GLYCERYL ACRYLATE/ACRYLIC ACID COPOLYMER、SORBITAN ISOSTEARATE、POLYSORBATE 60、BUTYLENE GLYCOL、1,2-HEXANEDIOL、IODOPROPYNYL BUTYLCARBAMATE、PVM/MA、COPOLYMER、PEG-90M

Warning.
1、For external use only, avoid contact with eyes when used
2、Keep out of reach of children

INDICATIONS AND USAGE

For Skin Whitonina Moieturizina Rriahtonina And Antinvidantl Indicatione- For whitonina moisturisino and hriohtonino facial ekinll

DOSAGE AND ADMINISTRATION

Apply the serum to your forehead, nose, cheeks, and chin, then gently pat it away with your fingers

Warning.
1、For external use only, avoid contact with eyes when used
2、Keep out of reach of children

ACTIVE INGREDIENT

Glutathione1%
KOJIC DIPALMITATE2%
HYDROLYZED COLLAGEN EXTRACT2%

PACKAGE LABEL

Active Ingredients
Glutathione1%
KOJIC DIPALMITATE2%
HYDROLYZED COLLAGEN EXTRACT2%

Uses：
For Skin Whitening, Moisturizing, Brightening And Antioxidant.
Indications: For whitening, moisturising and brightening facial skin.
The storage method：
Store sealed in a cool place and out of sunlight

Warning.
1、For external use only, avoid contact with eyes when used
2、Keep out of reach of children

Inactive ingredients：
AQUA、PROPYLENE GLYCOL、GLYCERETH-26、PENTAERYTHRITYL TETRAETHYLHEXANOATE、ETHYLHEXYL PALMITATE、GLYCERIN、CETEARYL ALCOHOL、HYDROXYETHYL ACRYLATE/SODIUM ACRYLOYLDIMETHYL TAURATE COPOLYMER、DMDM HYDANTOIN、XANTHAN GUM、AROMA、CETEARYL GLUCOSIDE、DISODIUM EDTA、GLYCERYL ACRYLATE/ACRYLIC ACID COPOLYMER、SORBITAN ISOSTEARATE、POLYSORBATE 60、BUTYLENE GLYCOL、1,2-HEXANEDIOL、IODOPROPYNYL BUTYLCARBAMATE、PVM/MA、COPOLYMER、PEG-90M